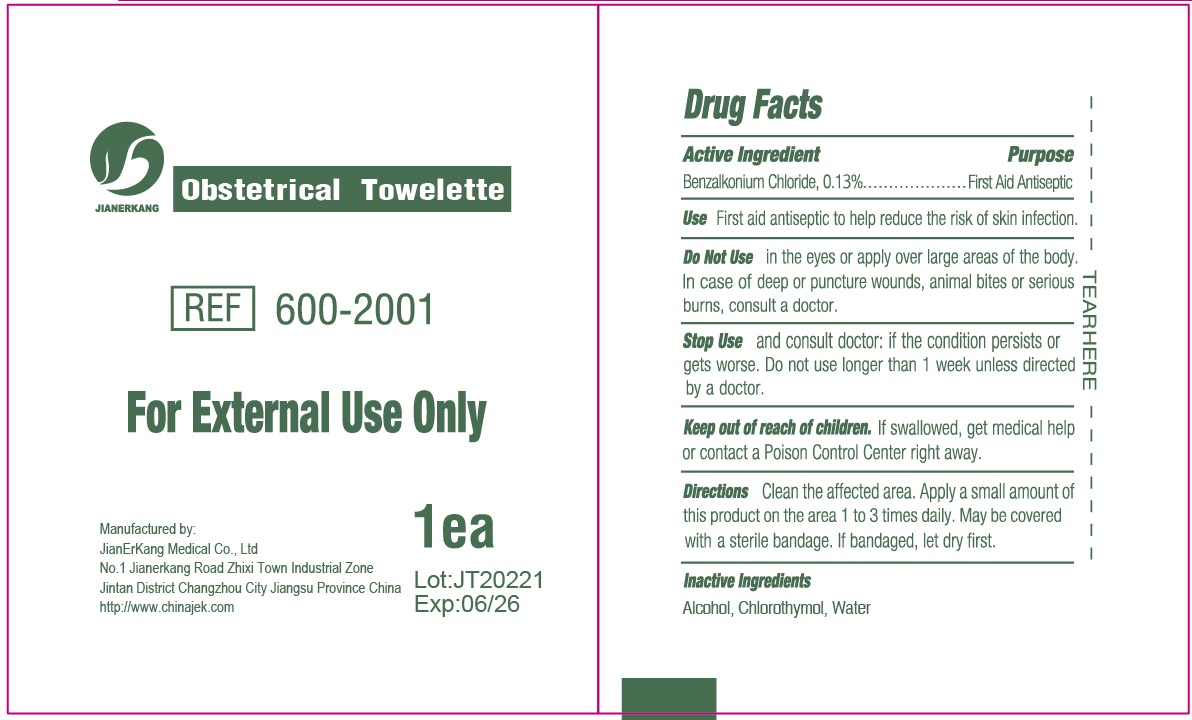 DRUG LABEL: Obstetrical Towelette
NDC: 34645-0015 | Form: CLOTH
Manufacturer: Jianerkang Medical Co., Ltd
Category: otc | Type: HUMAN OTC DRUG LABEL
Date: 20231023

ACTIVE INGREDIENTS: BENZALKONIUM CHLORIDE 1.3 mg/1 g
INACTIVE INGREDIENTS: ALCOHOL; CHLOROTHYMOL; WATER

Obstetrical Towelette

Active Ingredient

Benzalkonium Chloride, 0.13%

Purpose

First Aid Antiseptic

Use

First aid antiseptic to help reduce the risk of skin infection.

WARNINGS

For External Use Only

Do Not Use

in the eyes or apply over large areas of the body. In case of deep or puncture wounds, animal bites or serious burns, consult a doctor.

Stop Use

and consult doctor: if the condition persists or gets worse. Do not use longer than 1 week unless directed by a doctor.

Keep out of reach of children.

If swallowed, get medical help or contact a Poison Control Center right away.

Directions

Clean the affected area. Apply a small amount of this product on the area 1 to 3 times daily. May be covered with a sterile bandaged. If bandaged, let dry first.

Inactive Ingredients

Alcohol, Chlorothymol, Water